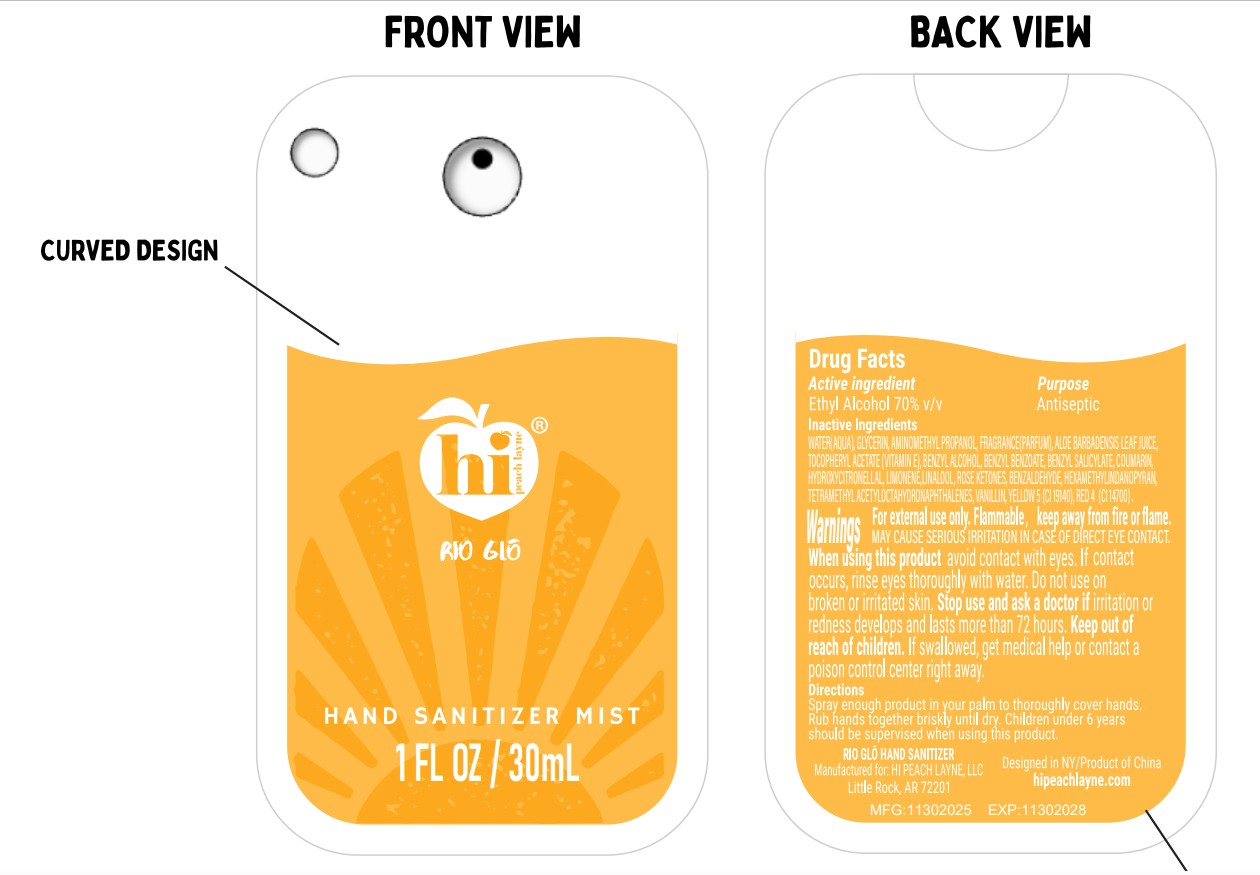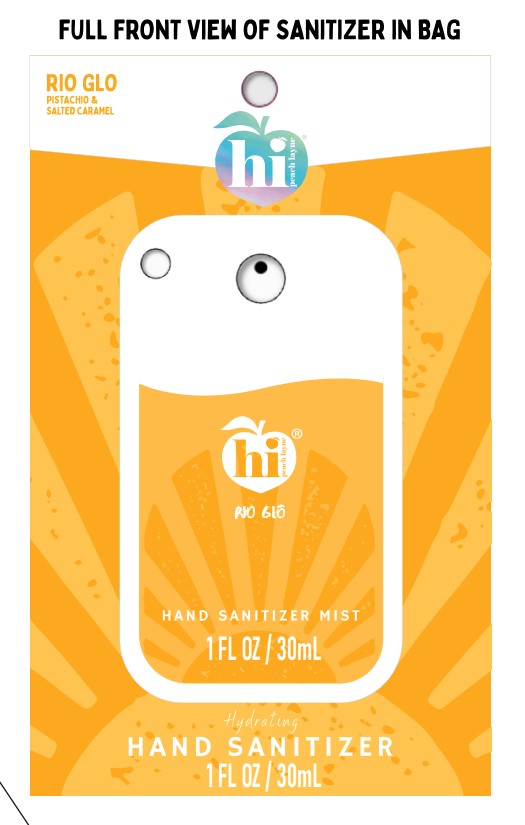 DRUG LABEL: hi peach layne
NDC: 73905-047 | Form: SPRAY
Manufacturer: ZHEJIANG JINGHUI COSMETICS SHARE CO.,LTD
Category: otc | Type: HUMAN OTC DRUG LABEL
Date: 20260115

ACTIVE INGREDIENTS: ALCOHOL 70 mL/100 mL
INACTIVE INGREDIENTS: FRAGRANCE 13576; LINALOOL; HYDROXYCITRONELLAL; YELLOW 5; AMINOMETHYL PROPANOL; COUMARIN; ALOE BARBADENSIS LEAF JUICE; HEXAMETHYLINDANOPYRAN; BENZALDEHYDE; .BETA.-DAMASCENONE; GLYCERIN; BENZYL SALICYLATE; WATER; BENZYL BENZOATE; BENZYL ALCOHOL; LIMONENE, (+/-)-; RED 4; TETRAMETHYL ACETYLOCTAHYDRONAPHTHALENES; ALPHA-TOCOPHEROL ACETATE; VANILLIN

1-RIO GLO HAND SANITIZER-73905-047-30ml

ACTIVE INGREDIENT

Ethyl Alcohol 70% v/v

PURPOSE

Antiseptic

INACTIVE INGREDIENT

WATERI(AQUA), GLYCERIN, AMINOMETHYL PROPANOL, FRAGRANCE(PARFUM), ALOE BARBADENSIS LEAF JUICE, TOCOPHERYL ACETATE(VTIAMIN E), BENZYL ALCOHOL,BENZYL BENZOATE, BENZYL SALICYLATE,COUMARIN, HYDROXYCITRONELLAL, LIMONENE,LINALOOL, ROSE KETONES, BENZALDEHYDE, HEXAMETHYLINDANOPYRAN, TETRAMETHYL ACETYLOCTAHYDRONAPHTHALENES, VANILLIN, YELLOW 5 (CI 19140), RED 4(CI 14700).

WARNINGS

For external use only. Flammable, keep away from fire or flame.

MAY CAUSE SERIOUS IRRITATION IN CASE OF DIRECT EYE CONTACT. When using this product avoid contact with eyes. If contact occurs, rinse eyes thoroughly with water. Do not use on broken or irritated skin. Stop use and ask a doctor if irritation or redness develops and lasts more than 72 hours.

Keep out of reach of children. If swallowed, get medical help or contact a poison control center right away.

INDICATIONS AND USAGE

Spray enough product in your palm to thoroughly cover hands. Rub hands together briskly until dry. Children under 6 years should be supervised when using this product.

DOSAGE AND ADMINISTRATION

Spray enough product in your palm to thoroughly cover hands. Rub hands together briskly until dry.